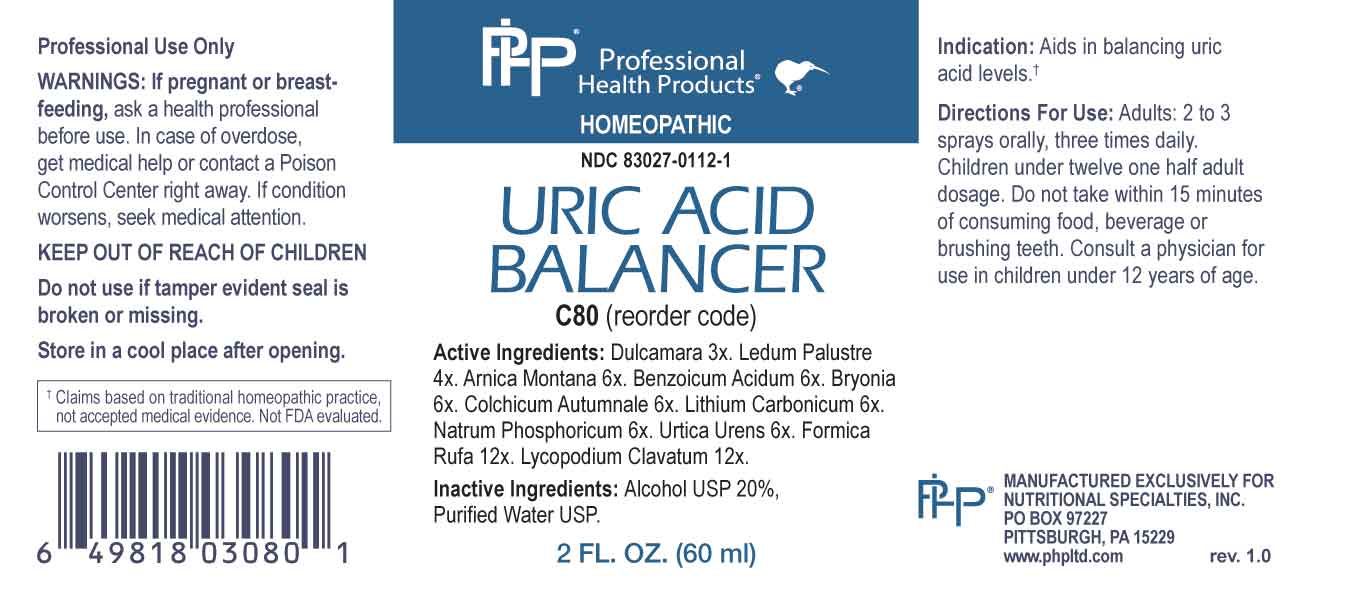 DRUG LABEL: Uric Acid Balancer
NDC: 83027-0112 | Form: SPRAY
Manufacturer: Nutritional Specialties, Inc.
Category: homeopathic | Type: HUMAN OTC DRUG LABEL
Date: 20231004

ACTIVE INGREDIENTS: SOLANUM DULCAMARA TOP 3 [hp_X]/1 mL; RHODODENDRON TOMENTOSUM LEAFY TWIG 4 [hp_X]/1 mL; ARNICA MONTANA WHOLE 6 [hp_X]/1 mL; BENZOIC ACID 6 [hp_X]/1 mL; BRYONIA ALBA ROOT 6 [hp_X]/1 mL; COLCHICUM AUTUMNALE BULB 6 [hp_X]/1 mL; LITHIUM CARBONATE 6 [hp_X]/1 mL; SODIUM PHOSPHATE, DIBASIC, HEPTAHYDRATE 6 [hp_X]/1 mL; URTICA URENS WHOLE 6 [hp_X]/1 mL; FORMICA RUFA 12 [hp_X]/1 mL; LYCOPODIUM CLAVATUM SPORE 12 [hp_X]/1 mL
INACTIVE INGREDIENTS: WATER; ALCOHOL

DRUG FACTS:

ACTIVE INGREDIENTS:

Dulcamara 3X, Ledum Palustre 4X, Arnica Montana 6X, Benzoicum Acidum 6X, Bryonia 6X, Colchicum Autumnale 6X, Lithium Carbonicum 6X, Natrum Phosphoricum 6X, Urtica Urens 6X, Formica Rufa 12X, Lycopodium Clavatum 12X.

PURPOSE:

Aids in balancing uric acid levels.†

†Claims based on traditional homeopathic practice, not accepted medical evidence. Not FDA evaluated.

WARNINGS:

Professional Use Only

If pregnant or breast-feeding, ask a health professional before use.

In case of overdose, get medical help or contact a Poison Control Center right away.

If condition worsens, seek medical attention.

KEEP OUT OF REACH OF CHILDREN

Do not use if tamper evident seal is broken or missing.

Store in a cool place after opening

KEEP OUT OF REACH OF CHILDREN:

In case of overdose, get medical help or contact a Poison Control Center right away.

DIRECTIONS:

Adults: 2 to 3 sprays orally, three times daily. Children under twelve one half adult dosage. Do not take within 15 minutes of consuming food, beverage or brushing teeth. Consult a physician for use in children under 12 years of age.

INDICATIONS:

Aids in balancing uric acid levels.†

†Claims based on traditional homeopathic practice, not accepted medical evidence. Not FDA evaluated.

INACTIVE INGREDIENTS:

Alcohol USP 20%, Purified Water USP.

QUESTIONS:

MANUFACTURED EXCLUSIVELY FOR

NUTRITIONAL SPECIALTIES, INC.

PO BOX 97227

PITTSBURG, PA 15229

www.phpltd.com

PACKAGE LABEL DISPLAY:

Professional

Health Products

HOMEOPATHIC

NDC 83027-0112-1

URIC ACID

BALANCER

2 FL. OZ (60 ml)